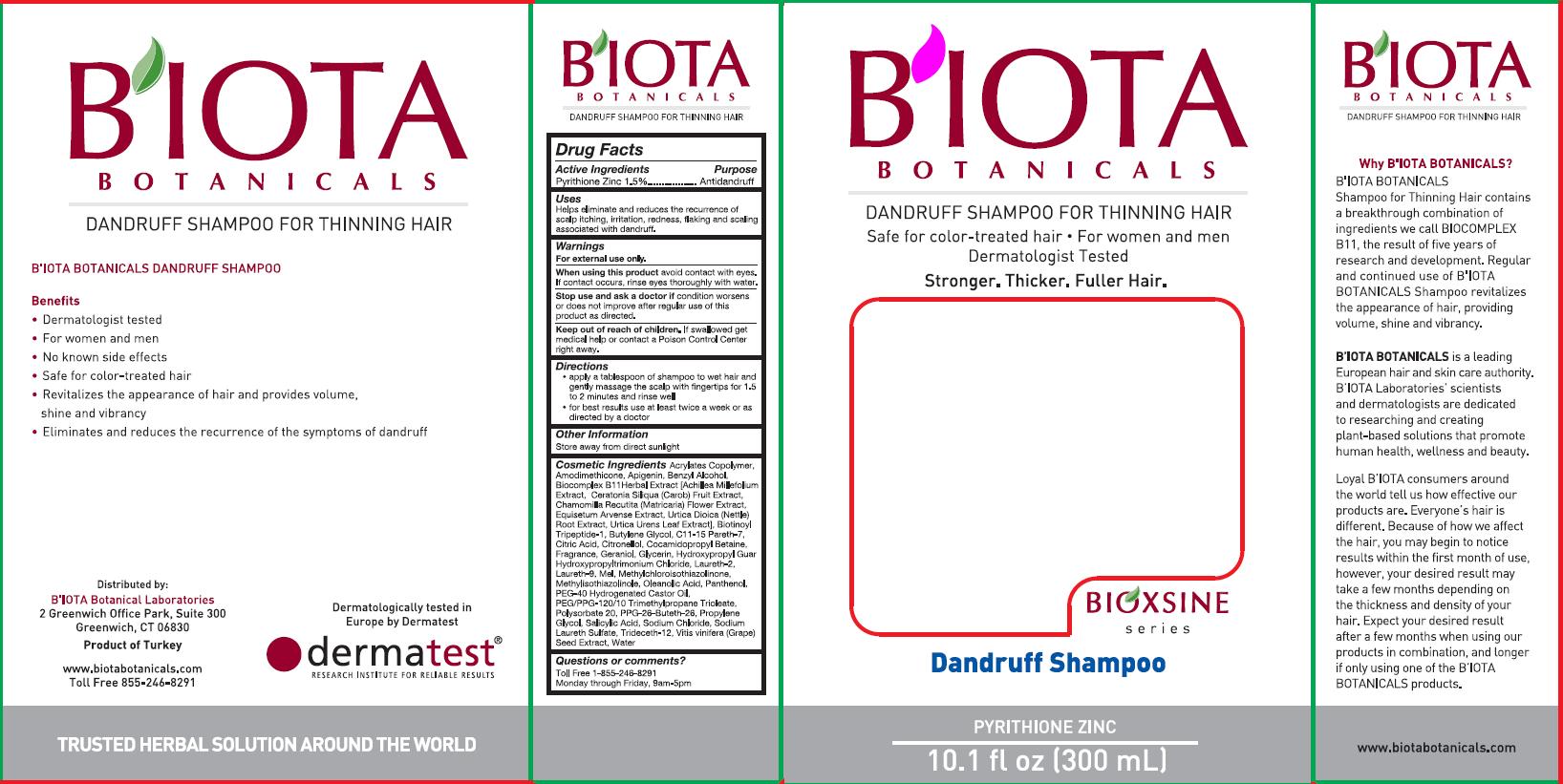 DRUG LABEL: Bioxsine Series 
NDC: 23637-001 | Form: SHAMPOO
Manufacturer: B'IOTA Laboratories
Category: otc | Type: HUMAN OTC DRUG LABEL
Date: 20111205

ACTIVE INGREDIENTS: PYRITHIONE ZINC 4.5 mL/300 mL
INACTIVE INGREDIENTS: APIGENIN; BENZYL ALCOHOL; ACHILLEA MILLEFOLIUM; CAROB; CHAMOMILE; EQUISETUM ARVENSE TOP; URTICA DIOICA ROOT; URTICA URENS LEAF; BUTYLENE GLYCOL; CITRIC ACID MONOHYDRATE; .BETA.-CITRONELLOL, (R)-; COCAMIDOPROPYL BETAINE; GERANIOL; GLYCERIN; LAURETH-2; POLIDOCANOL; HONEY; METHYLCHLOROISOTHIAZOLINONE; METHYLISOTHIAZOLINONE; OLEANOLIC ACID; PANTHENOL; POLYOXYL 40 HYDROGENATED CASTOR OIL; POLYSORBATE 20; PROPYLENE GLYCOL; SALICYLIC ACID; SODIUM CHLORIDE; SODIUM LAURETH SULFATE; TRIDECETH-12; VITIS VINIFERA SEED; WATER

ACTIVE INGREDIENT

Pyrithione Zinc 1.5%

PURPOSE

Antidandruff

INDICATIONS AND USAGE

Helps eliminate and reduces the recurrence of scalp itching, irritation, redness, flaking and scaling associated with dandruff.

WARNINGS

For external use only.

When using this product avoid contact with eyes. If contact occurs, rinse eyes thoroughly with water.

Stop use and ask a doctor if condition worsens or does not improve after regular use of this product as directed.

Keep out of reach of children. If swallowed get medical help or contact a Poison Control Center right away.

Directions

- apply a tablespoon of shampoo to wet hair and gently massage the scalp with fingertips for 1.5 to 2 minutes and rinse well
- for best results use at least twice a week or as directed by a doctor

STORAGE AND HANDLING

Store away from direct sunlight

INACTIVE INGREDIENT

Cosmetic Ingredients Acrylates Copolymer, Amodimethicone, Apigenin, Benzyl Alcohol, Biocomplex B11 Herbal Extract [Achillea Millefolium Extract], Ceratonia Siliqua (Carob) Fruit Extract, Chamomilla Recutita (Matricaria) Flower Extract, Equisetum Arvense Extract, Urtica Dioica (Nettle) Root Extract, Urtica Urens Leaf Extract, Biotinoyl Tripeptide-1, Butylene Glycol, C11-15 Pareth-7, Citric Acid, Citronellol, Cocamidopropyl Betaine, Fragrance, Geraniol, Glycerin, Hydroxypropyl Guar Hydroxyproplytrimonium Chloride, Laureth-2, Laureth-9, Mel, Methylchloroisothiazolinone, Methylisothiazolinole, Oleanolic Acid, Panthenol, PEG-40 Hydrogenated Castor Oil, PEG/PPG-120/10 Trimethylpropane Trioleate, Polysorbate 20, PPG-26-Buteth-26, Propylene Glycol, Salicylic Acid, Sodium Chloride, Sodium Laureth Sulfate, Trideceth-12, Vitis Vinifera (Grape) Seed Extract, Water

QUESTIONS

Toll Free 1-855-246-8291 Monday through Friday, 9am-5pm

DESCRIPTION

B'IOTA Botanicals Dandruff Shampoo

Benefits

- Dermatologist tested
- For women and men
- No known side effects
- Safe for color-treated hair
- Revitalizes the appearance of hair and provides volume, shine and vibrancy
- Eliminates and reduces the recurrence of the symptoms of dandruff

Distributed by:
B'IOTA Botanical Laboratories
2 Greenwich Office Park, Suite 300
Greenwich, CT 06830
Product of Turkey
www.biotabotanicals.com
Toll Free 855-246-8291